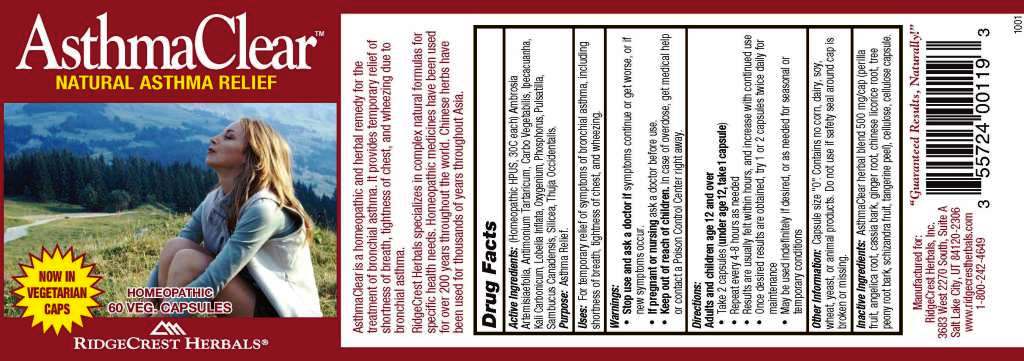 DRUG LABEL: AsthmaClear
NDC: 57520-0422 | Form: CAPSULE
Manufacturer: Apotheca Company
Category: homeopathic | Type: HUMAN OTC DRUG LABEL
Date: 20110509

ACTIVE INGREDIENTS: ANTIMONY POTASSIUM TARTRATE 30 [hp_C]/1 1; ACTIVATED CHARCOAL 30 [hp_C]/1 1; IPECAC 30 [hp_C]/1 1; POTASSIUM CARBONATE 30 [hp_C]/1 1; LOBELIA INFLATA 30 [hp_C]/1 1; PHOSPHORUS 30 [hp_C]/1 1; PULSATILLA VULGARIS 30 [hp_C]/1 1; SAMBUCUS NIGRA SUBSP. CANADENSIS FLOWERING TOP 30 [hp_C]/1 1; SILICON DIOXIDE 30 [hp_C]/1 1; THUJA OCCIDENTALIS LEAFY TWIG 30 [hp_C]/1 1; AMBROSIA ARTEMISIIFOLIA 30 [hp_C]/1 1; OXYGEN 30 [hp_C]/1 1
INACTIVE INGREDIENTS: ANGELICA ARCHANGELICA ROOT; CHINESE CINNAMON; GINGER; CELLULOSE, MICROCRYSTALLINE; SCHISANDRA CHINENSIS FRUIT; TANGERINE; GLYCYRRHIZA URALENSIS; PAEONIA SUFFRUTICOSA ROOT; PERILLA FRUTESCENS FRUIT

AsthmaClear

ACTIVE INGREDIENT

ACTIVE INGREDIENTS: Ambrosia artemisiaefolia 30C, Antimonium tartaricum 30C, Carbo vegetabilis 30C, Ipecacuanha 30C, Kali carbonicum 30C, Lobelia inflata 30C, Oxygenium 30C, Phosphorus 30C, Pulsatilla 30C, Sambucus canadensis 30C, Silicea 30C, Thuja occidentalis 30C.

PURPOSE

USES: For temporary relief of symptoms of bronchial asthma, including shortness of breath, tightness of chest, and wheezing.

WARNINGS:

Stop use and ask a doctor if symptoms continue or get worse, or if new symptoms occur.

If pregnant or nursing, ask a doctor before use.

Keep out of reach of children. In case of overdose, get medical help or contact a Poison Control Center right away.

DIRECTIONS:

Adults and children age 12 and over

Take 2 capsules (under age 12, take 1 capsule)

Repeat every 4-8 hours as needed

Results are usually felt within hours, and increase with continued use

Once desired results are obtained, try 1 or 2 capsules twice daily for maintenance

May be used indefinitely if desired, or as needed for seasonal or temporary conditions.

Other information: Capsule size "0". Contains no corn, soy, wheat, yeast, or animal products. Do not use if safety seal around cap is broken or missing.

Asthma Clear is a homeopathic and herbal remedy for the treatment of bronchial asthma. It provides temporary relief of shortness of breath, tightness of chest, and wheezing due to bronchial asthma.

RidgeCrest Herbals specializes in complex natural formulas for specific health needs, Homeopathic medicines have been used for over 200 years throughout the world. Chinese herbs have been used for thousands of years throughout Asia.

INACTIVE INGREDIENT

INACTIVE INGREDIENTS: Asthma Clear herbal blend 500 mg/cap (perilla fruit, angelica root, cassia bark, ginger root, chinese licorice root, tree peony root bark, schizandra fruit, tangerine peel) cellulose, cellulose capsule.

KEEP OUT OF REACH OF CHILDREN: In case of overdose, get medical help or contact a Poison Control Center right away.

INDICATIONS AND USAGE

USES: For temporary relief of symptoms of bronchial asthma, including shortness of breath, tightness of chest, and wheezing.

QUESTIONS

Manufactured for:

RidgeCrest Herbals, Inc.

3683 West 2270 South, Suite A

Salt Lake City, UT, 84120-2306

www.ridgecrestherbals.com

1-800-242-4649

PACKAGE LABEL

AsthmaClear

NATURAL ASTHMA RELIEF

NOW IN VEGETARIAN CAPS

HOMEOPATHIC

60 VEG CAPSULES

RIDGECREST HERBALS